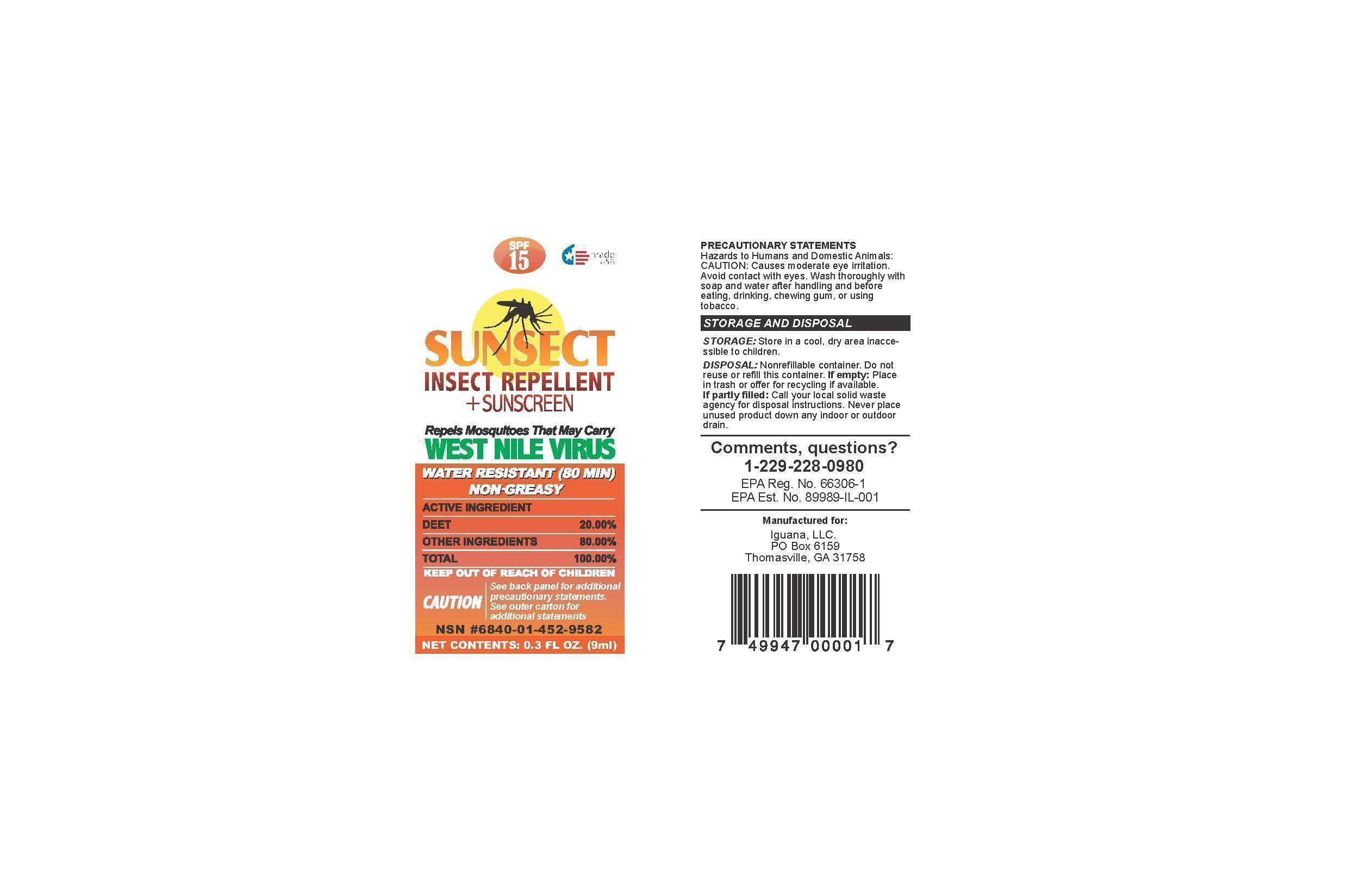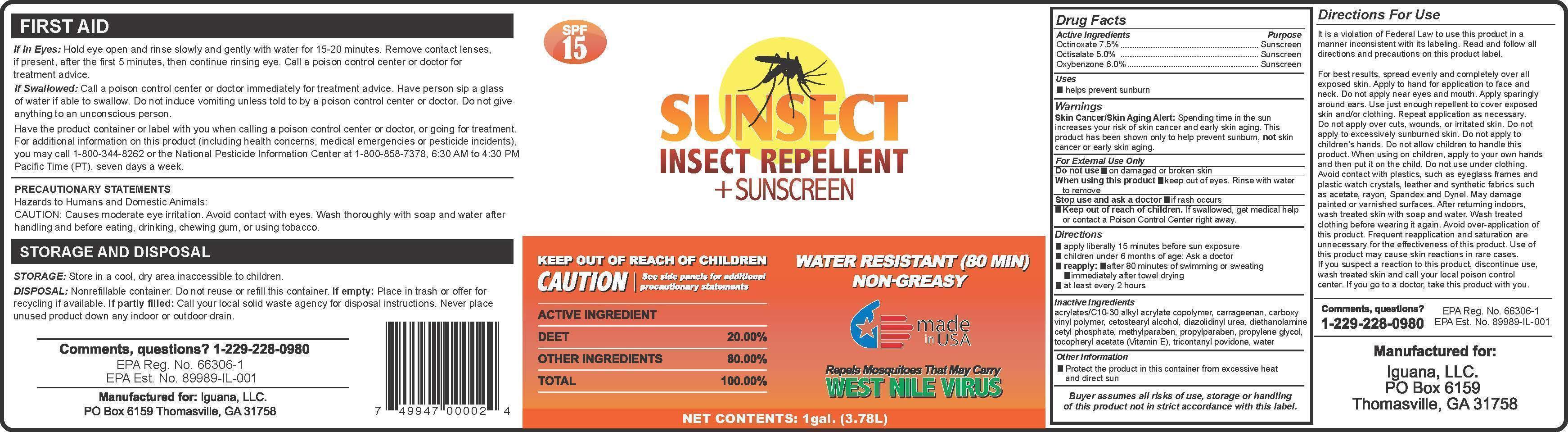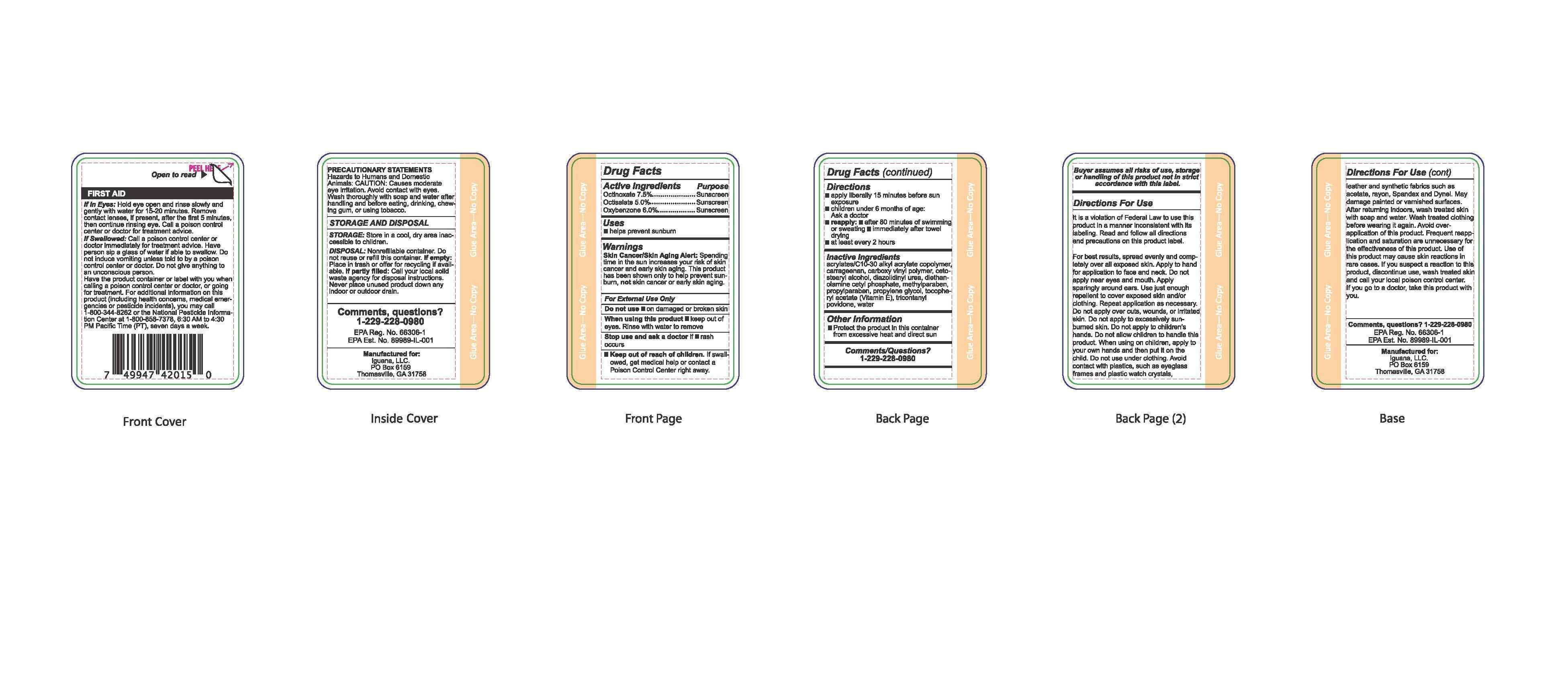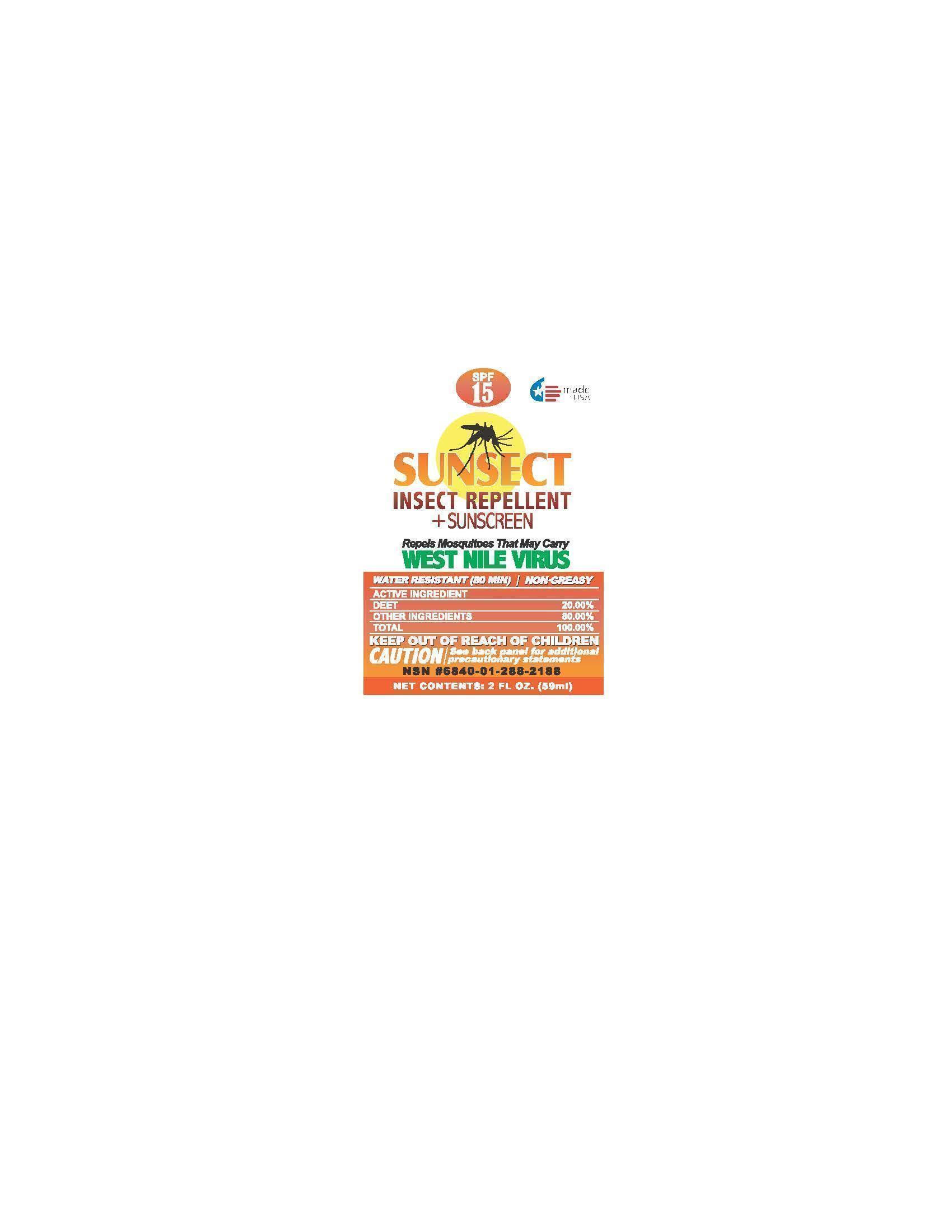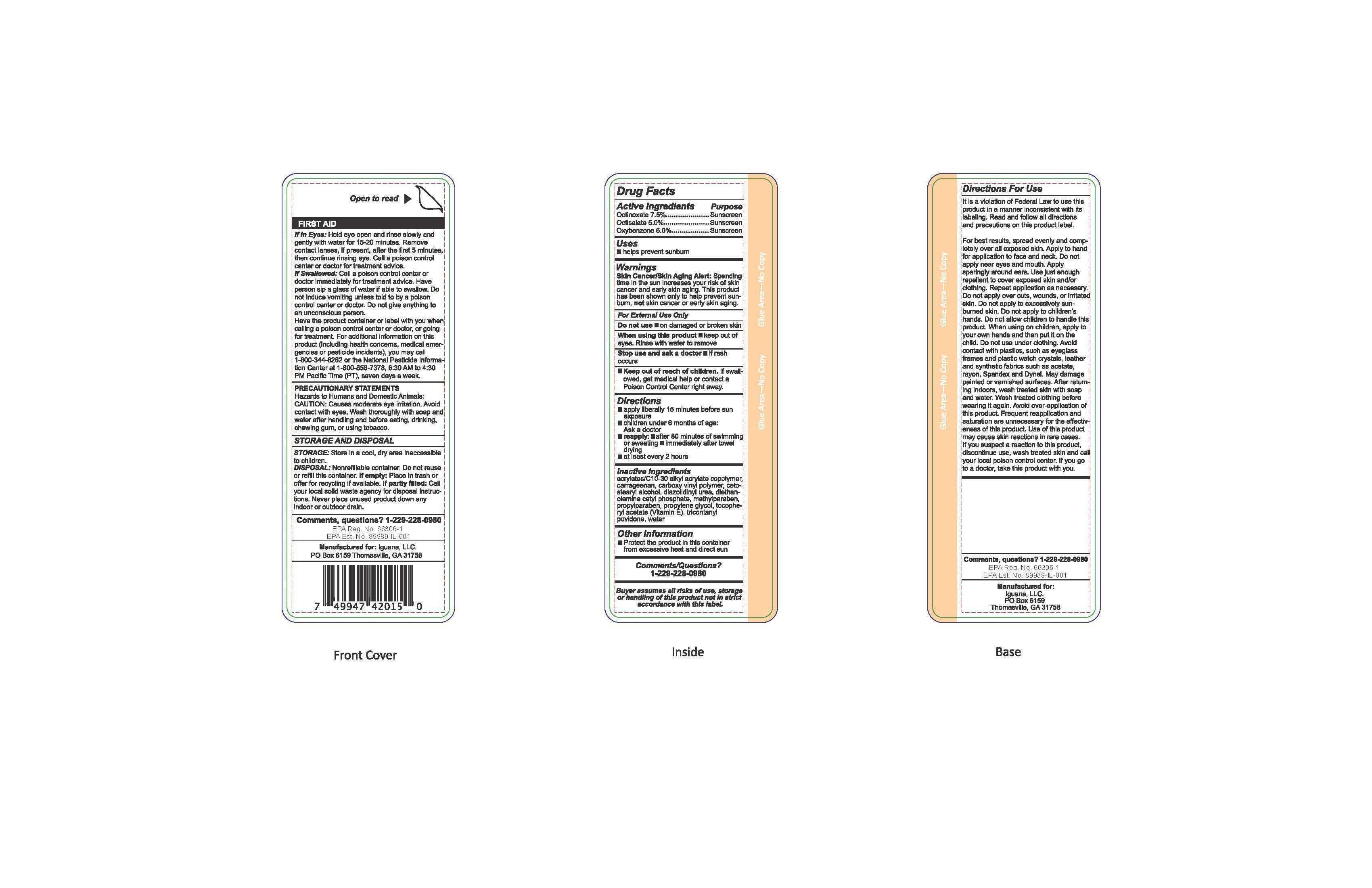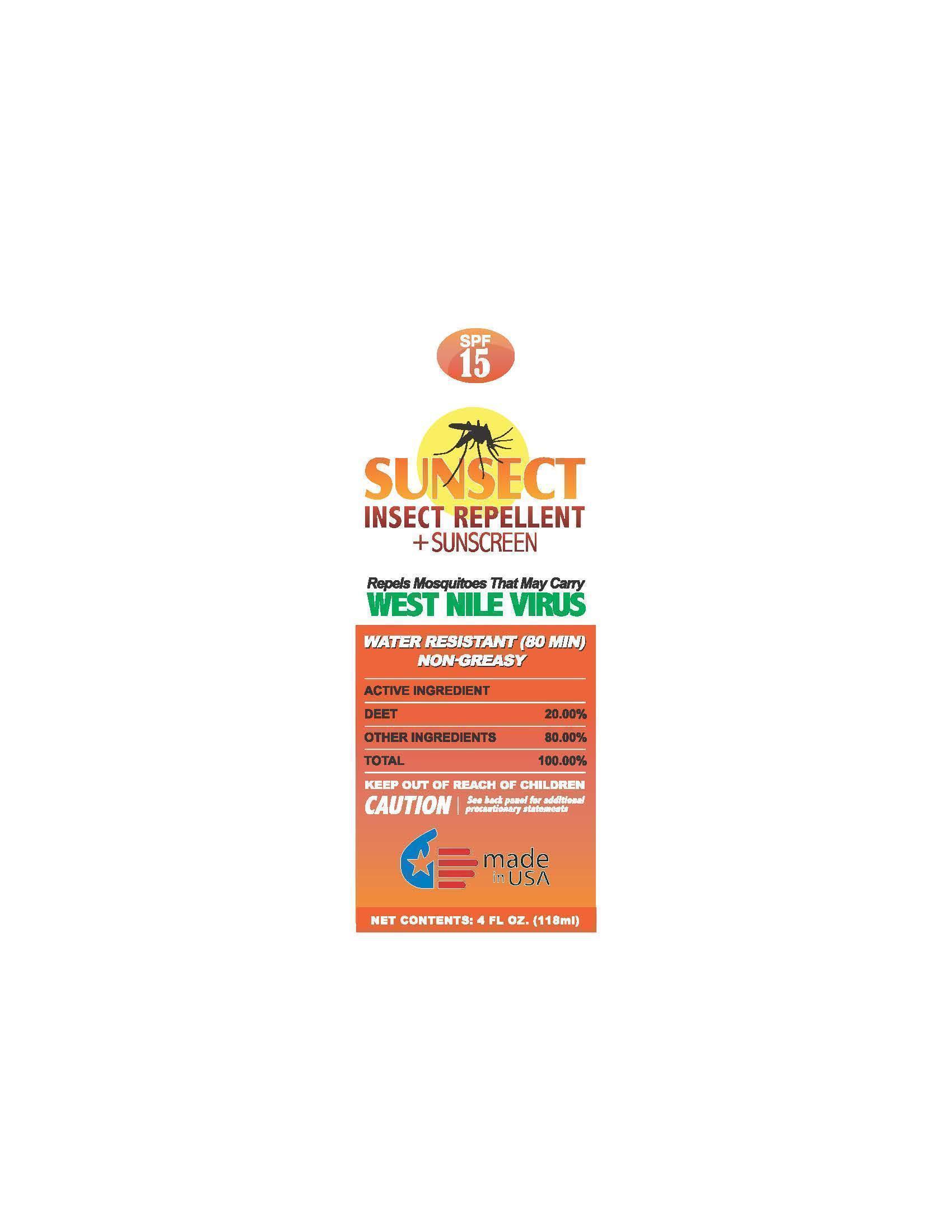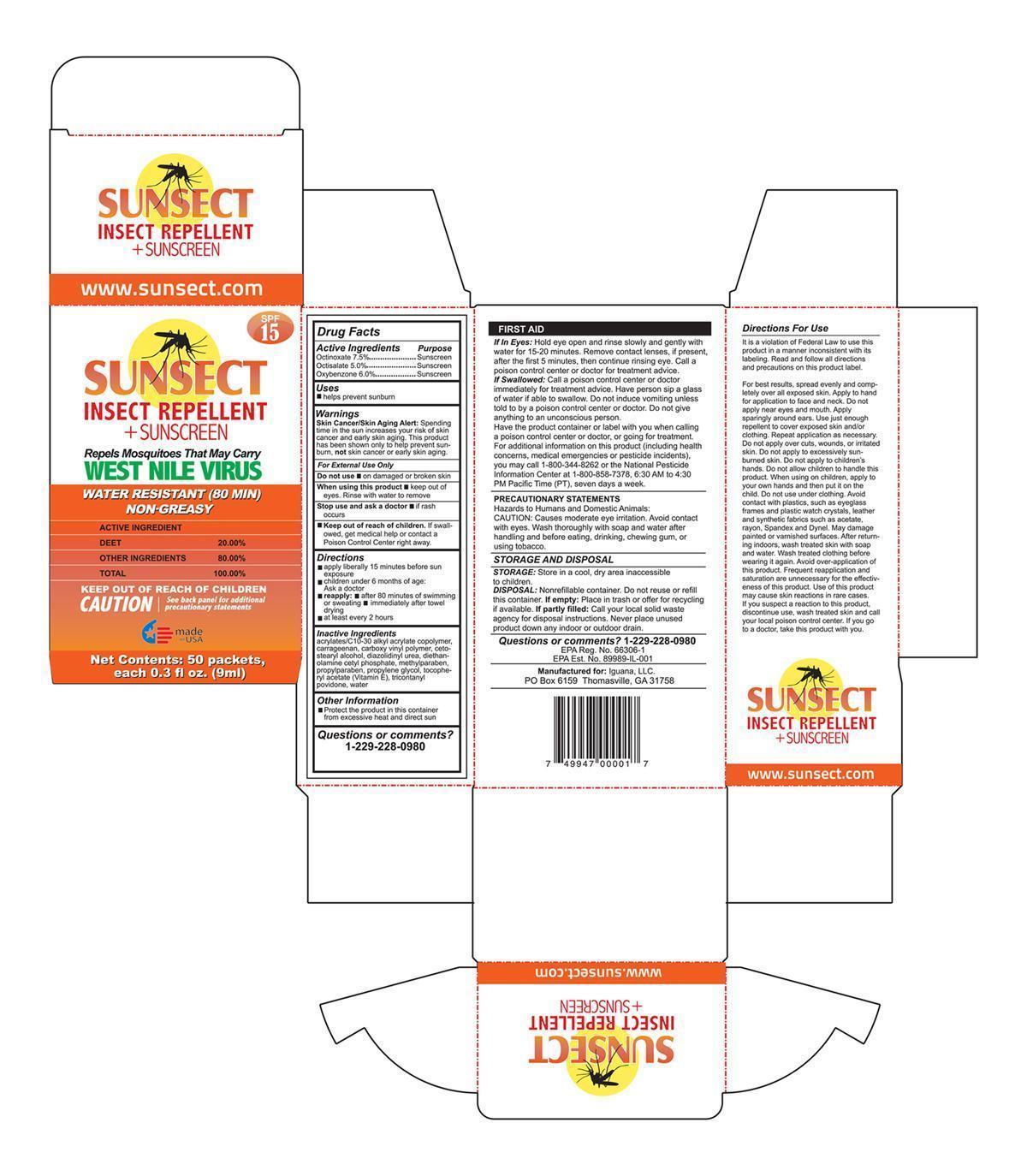 DRUG LABEL: Sunsect Insect Repellent Sunscreen
NDC: 57595-001 | Form: LOTION
Manufacturer: Iguana LLC
Category: otc | Type: HUMAN OTC DRUG LABEL
Date: 20150620

ACTIVE INGREDIENTS: OCTISALATE 5 g/100 g; OCTINOXATE 7.5 g/100 g; OXYBENZONE 6 g/100 g; DIETHYLTOLUAMIDE 20 g/100 g
INACTIVE INGREDIENTS: CARBOMER COPOLYMER TYPE B (ALLYL PENTAERYTHRITOL CROSSLINKED); CARBOMER HOMOPOLYMER TYPE C; PROPYLENE GLYCOL; Carrageenan; CETOSTEARYL ALCOHOL; DIETHANOLAMINE CETYL PHOSPHATE; TRICONTANYL POVIDONE; ALPHA-TOCOPHEROL ACETATE; WATER; DIAZOLIDINYL UREA; METHYLPARABEN; PROPYLPARABEN; CITRONELLA OIL

Drug Facts

Active Ingredients

Octinoxate: 7.5%
Oxybenzone: 6%
Octisalate: 5%

Purpose

Sunscreen

Uses

- helps prevent sunburn

Warnings

Skin Cancer/Skin Aging Alert: Spending time in the sun increases your risk of skin cancer and early skin aging. This product has been shown only to help prevent sunbrun, not skin cancer or early skin aging.

For external use only. Do not use on damaged or broken skin. When using this product keep out of eyes. Rinse with water to remove. Stop use and ask a doctor if rash occurs. Keep out of the reach of children. If swallowed, get medical help or contact a Poison Control Center right away.

Directions

- apply liberally 15 minutes before sun exposure
- children under 6 months of age: Ask a doctor
- reapply: after 80 minutes of swimming or sweating
- immediately after towel drying
- at least every 2 hours

Other Information

- Protect the product in this container from excessive heat and direct sun

Inactive Ingredients

acrylates/C10-30 alkyl acrylate copolymer, carrageenan, carboxy vinyl polymer, cetostearyl alcohol, diazolidinyl urea, diethanolamine cetyl phosphate, methylparaben, propylparaben, propylene glycol, tocopheryl acetate (Vitamin E), tricontanyl povidone, water

Comments/Questions?

1-229-228-0980